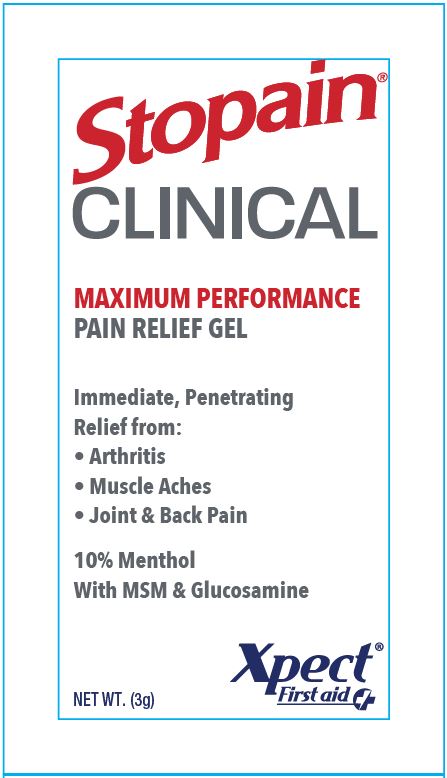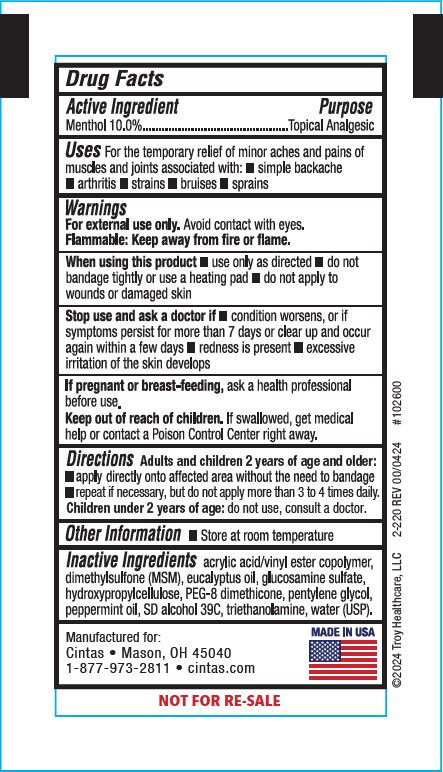 DRUG LABEL: Xpect Stopain Clinical
NDC: 42961-256 | Form: GEL
Manufacturer: Cintas Corporation
Category: otc | Type: HUMAN OTC DRUG LABEL
Date: 20260217

ACTIVE INGREDIENTS: MENTHOL 100 mg/1 g
INACTIVE INGREDIENTS: ACRYLIC ACID; DIMETHYL SULFONE; EUCALYPTUS OIL; GLUCOSAMINE SULFATE; HYDROXYPROPYL CELLULOSE, UNSPECIFIED; PEG-8 DIMETHICONE; PENTYLENE GLYCOL; PEPPERMINT OIL; TROLAMINE; WATER; ALCOHOL

Xpect Stopain Clinical Maximum Performance Pain Relief

Active Ingredient

Menthol 10.0%

Purpose

Topical Analgesic

Uses

For the temporary relief of minor aches and pains of muscles and joints associated with:

- simple backache
- arthritis
- strains
- bruises
- sprains

Warnings

For external use only. Avoid contact with eyes.

Flammable: Keep away from fire or flame.

When using this product

- use only as directed
- do not bandage tightly or use a heating pad
- do not apply to wounds or damaged skin

Stop use and ask a doctor if

- condition worsens, or if symptoms persist for more than 7 days or clear up and occur again within a few days
- redness is present
- excessive irritation of the skin develops

PREGNANCY OR BREAST FEEDING

If pregnant or breast-feeding, ask a health professional before use.

Keep out of reach of children. If swallowed, get medical help or contact a Poison Control Center right away.

Directions

Adults and children 2 years of age and older:

- apply directly onto affected area without the need to bandage
- repeat if necessary, but do not apply more than 3 to 4 times daily

Children under 2 years of age: do not use, consult a doctor.

Other Information

- Store at room temperature

Inactive Ingredients

acrylic acid/vinyl ester copolymer, dimethylsulfone (MSM), eucalyptus oil, glucosamine sulfate, hydroxypropylcellulose, PEG-8 dimethicone, pentylene glycol, peppermint oil, SD alcohol 39C, triethanolamine, water (USP).

Principal Display Panel 42961-256-01

Stopain® Clinical

Maximum Performance Pain Relief Gel

Immediate, Penetrating Relief from:

- Arthritis
- Muscle Aches
- Joint & Back Pain

10% Menthol With MSM & Glucosamine

NET WT. (3g)

Xpect® First aid

Manufactured for: Cintas • Mason, OH 45040

1-877-973-2811 • cintas.com

MADE IN USA

NOT FOR RE-SALE

©2024 Troy Healthcare, LLC 2-220 REV 00/0424 #102600